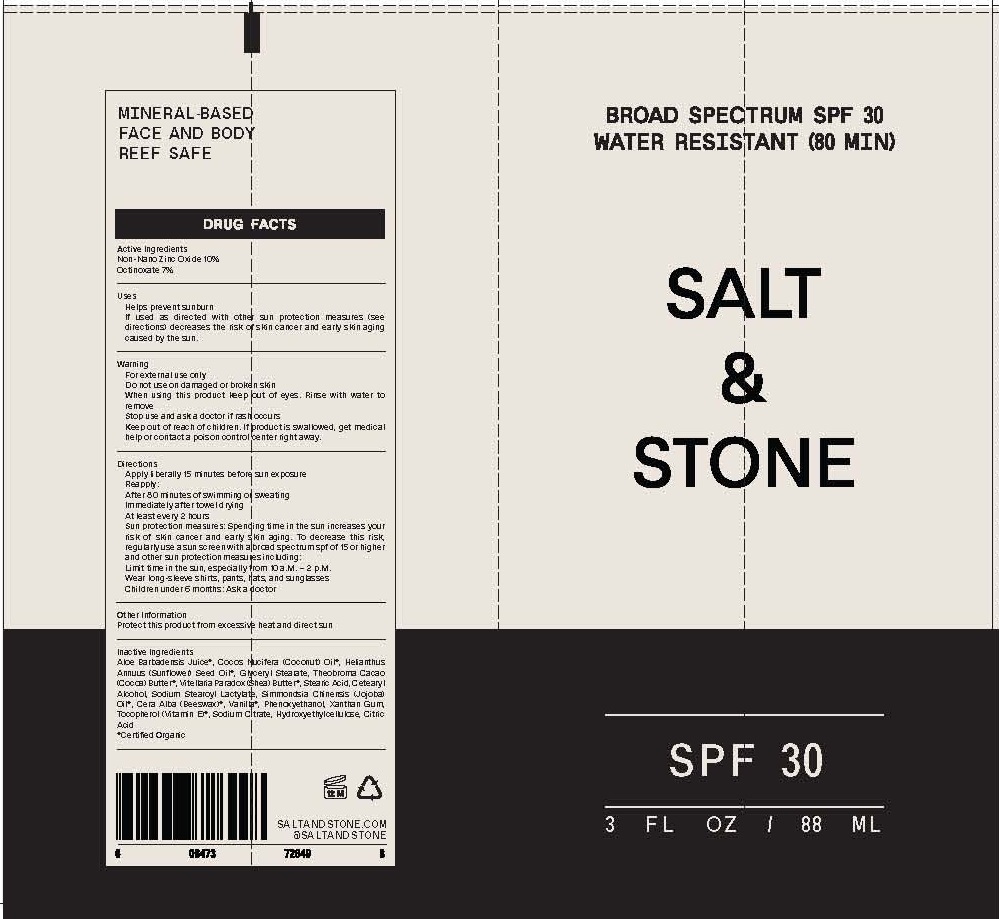 DRUG LABEL: PREMIUM SUNSCREEN
NDC: 71585-102 | Form: LOTION
Manufacturer: SALT AND STONE
Category: otc | Type: HUMAN OTC DRUG LABEL
Date: 20190411

ACTIVE INGREDIENTS: ZINC OXIDE 10 g/100 mL; OCTINOXATE 7 g/100 mL
INACTIVE INGREDIENTS: ALOE VERA LEAF; COCONUT OIL; SUNFLOWER OIL; GLYCERYL MONOSTEARATE; COCOA BUTTER; SHEA BUTTER; STEARIC ACID; CETOSTEARYL ALCOHOL; SODIUM STEAROYL LACTYLATE; JOJOBA OIL; YELLOW WAX; VANILLA; PHENOXYETHANOL; XANTHAN GUM; .ALPHA.-TOCOPHEROL ACETATE; SODIUM CITRATE; HYDROXYETHYL CELLULOSE (100 MPA.S AT 2%); ANHYDROUS CITRIC ACID

MINERAL BASED SALT & STONE PREMIUM SUNSCREEN SPF-30

ACTIVE INGREDIENTS

ZINC OXIDE 10%

OCTINOXATE 7%

PURPOSE

SUNSCREEN

USES

- HELPS PREVENT SUNBURN
- IF USED AS DIRECTED WITH OTHER SUN PROTECTION MEASURES (SEE DIRECTIONS) DESCREASES THE RISK OF SKIN CANCER AND EARLY AGING CAUSED BY THE SUN.

WARNINGS

FOR EXTERNAL USE ONLY.

DO NOT USE ON DAMAGED OR BROKEN SKIN.

WHEN USING THIS PRODUCT KEEP OUT OF EYES. RINSE WITH WATER TO REMOVE.

STOP USE AND ASK A DOCTOR IF RASH OCCURS.

KEEP OUT OF REACH OF CHILDREN. IF PRODUCT IS SWALLOWED, GET MEDICAL HELP OR CONTACT A POISON CONTROL CENTER RIGHT AWAY.

DIRECTIONS

- APPLY LIBERALLY 15 MINUTES BEFORE SUN EXPOSURE.

REAPPLY:

- AFTER 80 MINUTES OF SWIMMING OR SWEATING
- IMMEDIATELY AFTER TOWEL DRYING
- AT LEAST EVERY 2 HOURS

SUN PROTECTION MEASURES. SPENDING TIME IN THE SUN INCREASES YOUR RISK OF SKIN CANCER AND EARLY SKIN AGING. TO DECREASE THIS RISK, REGULARLY USE A SUN SCREEN WITH A BROAD SPECTRUM OF SPF 15 OR HIGHER AND OTHER SUN PROTECTION MEASURES INCLUDING:

- LIMIT TIME IN THE SUN, FROM 10 A.M. - 2 P.M.
- WEAR LONG-SLEEVE SHIRTS, PANTS, HATS, AND SUNGLASSES
- CHILDREN UNDER 6 MONTHS: ASK A DOCTOR

INACTIVE INGREDIENTS

* ALOE BARBADENSIS JUICE, * COCOS NUCIFERA (COCONUT) OIL, * HELIANTHUS ANNUUS (SUNFLOWER) OIL, GLYCERYL STEARATE, * THEOBROMA CACAO (COCOA) BUTTER, * VITELLARIA PARADOX (SHEA) BUTTER, STEARIC ACID, CETEARYL ALCOHOL, SODIUM STEARYL LACTATE, * SIMMONDSIA CHINENSIS (JOJOBA) OIL, * CERA ALBA (BEESWAX), * VANILLA, PHENOXYETHANOL, XANTHAN GUM, * TOCOPHEROL (VITAMIN E), SODIUM CITRATE, HYDROXYETHYLCELLULOSE, CITRIC ACID

* CERTIFIED ORGANIC

OTHER INFORMATION

- PROTECT THIS PRODUCT FROM EXCESSIVE HEAT AND DIRECT SUN

QUESTIONS OR COMMENTS?

CALL TOLL FREE 888 952 4250